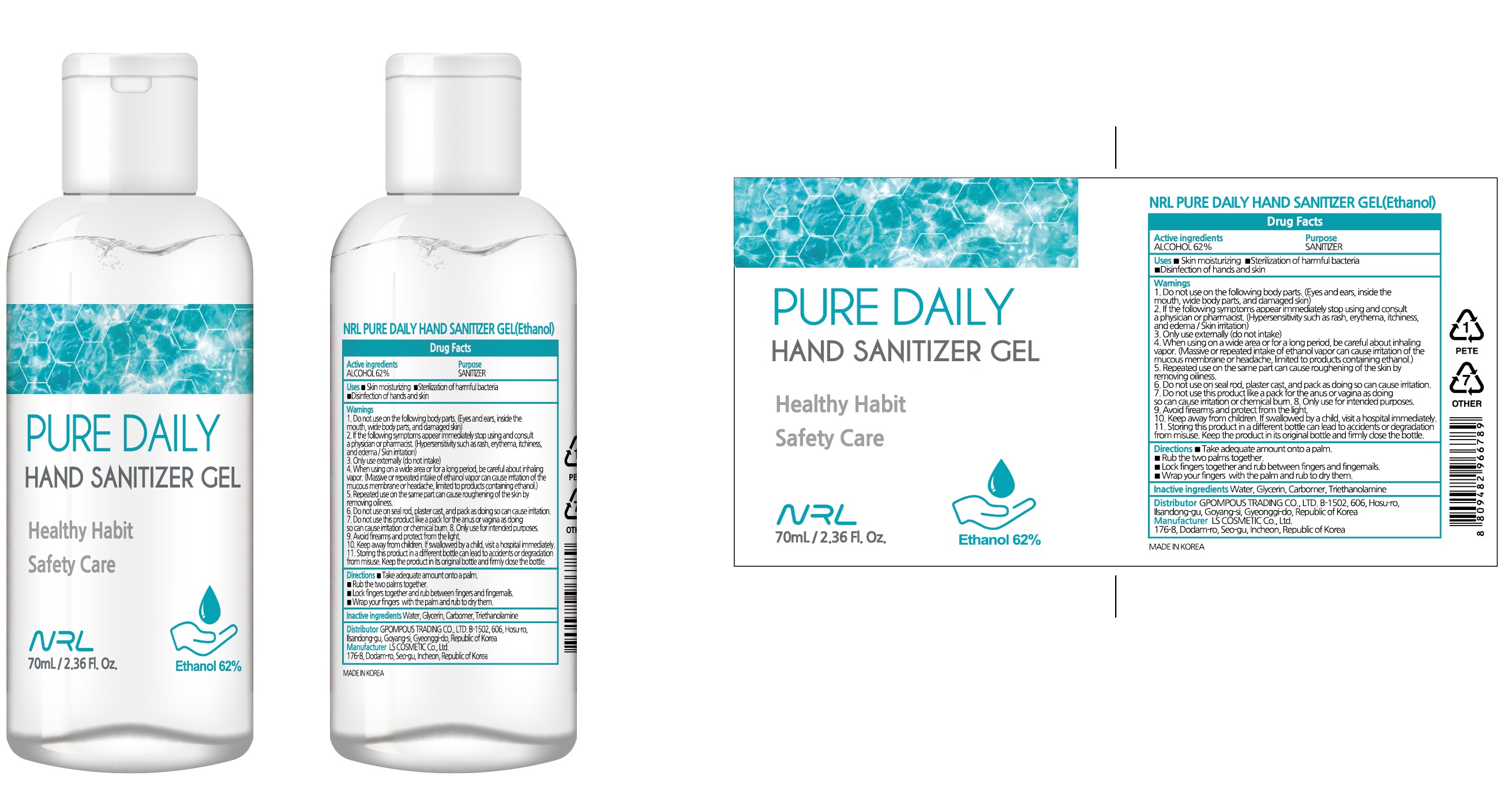 DRUG LABEL: NRL PURE DAILY HAND SANITIZER
NDC: 74083-010 | Form: GEL
Manufacturer: Gpompous Trading Co., Ltd.
Category: otc | Type: HUMAN OTC DRUG LABEL
Date: 20200408

ACTIVE INGREDIENTS: ALCOHOL 43.4 g/70 mL
INACTIVE INGREDIENTS: Water; GLYCERIN; CARBOMER HOMOPOLYMER, UNSPECIFIED TYPE; TROLAMINE

ACTIVE INGREDIENT

Active ingredients: ALCOHOL 62.0%

INACTIVE INGREDIENT

Inactive Ingredients:

Water, Glycerin, Carbomer, Triethanolamine

PURPOSE

Purpose: SANITIZER

WARNINGS

1. Do not use on the following body parts. (Eyes and ears, inside the mouth, wide body parts, and damaged skin)
2. If the following symptoms appear, immediately stop using and consult a physician or pharmacist. (Hypersensitivity such as rash, erythema, itchiness, and edema / Skin irritation)
3. Only use externally (do not intake)
4. When using on a wide area or for a long period, be careful about inhaling vapor. (Massive or repeated intake of ethanol vapor can cause irritation of the mucous membrane or headache, limited to products containing ethanol.)
5. Repeated use on the same part can cause roughening of the skin by removing oiliness.
6. Do not use on seal rod, plaster cast, and pack as doing so can cause irritation.
7. Do not use this product like a pack for the anus or vagina as doing so can cause irritation or chemical burn.
8. Only use for intended purposes.
9. Avoid firearms and protect from the light.
10. Keep away from children. If swallowed by a child, visit a hospital immediately.
11. Storing this product in a different bottle can lead to accidents or degradation from misuse. Keep the product in its original bottle and firmly close the bottle.
12. Do not use expired sanitary aids.

KEEP OUT OF REACH OF CHILDREN

Keep away from children. If swallowed by a child, visit a hospital immediately.

Uses

■ Skin moisturizing
■ Sterilization of harmful bacteria
■ Disinfection of hands and skin

Directions

■ Take adequate amount onto a palm.
■ Rub the two palms together.
■ Lock fingers together and rub between fingers and fingernails.
■ Wrap your fingers with the palm and rub to dry them.